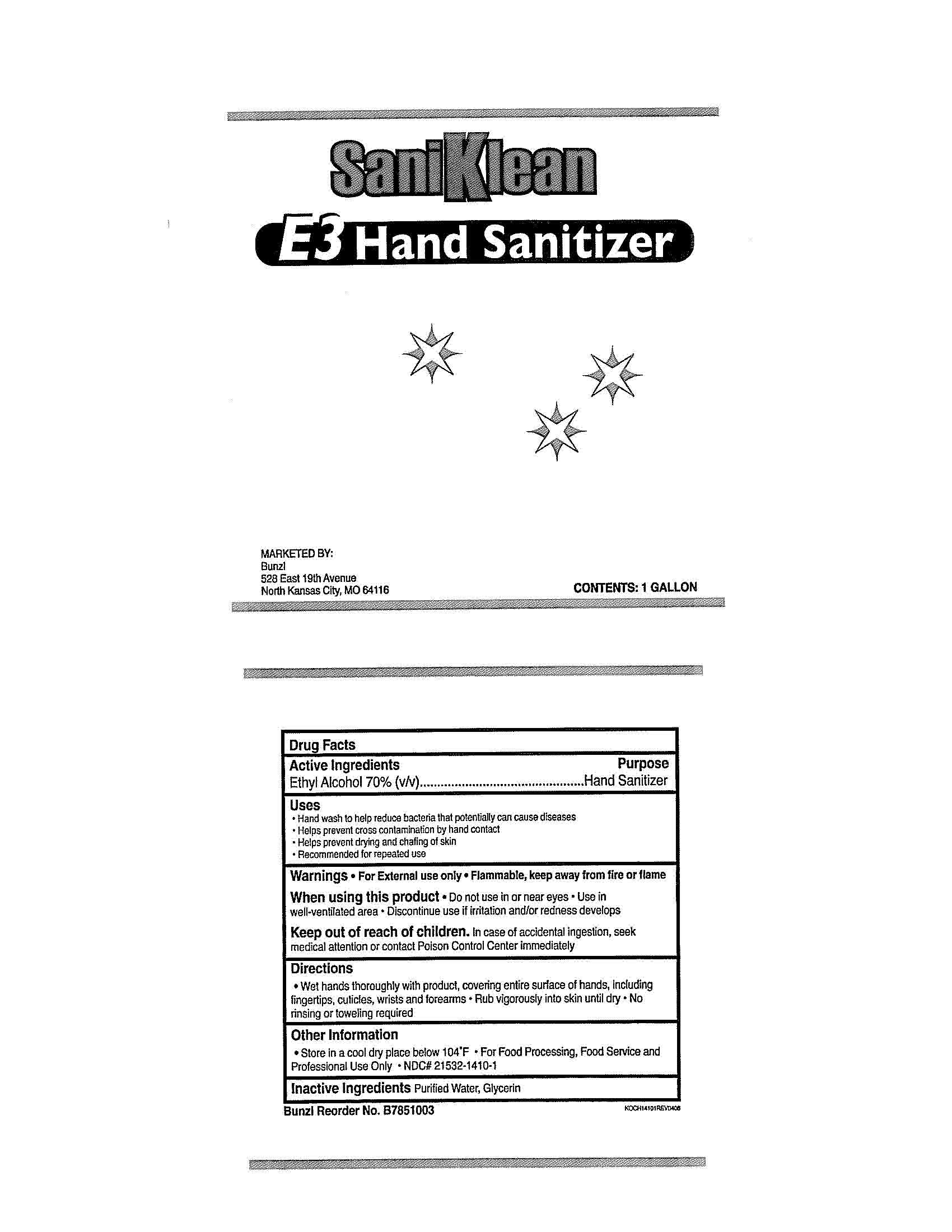 DRUG LABEL: SaniKlean E3 Hand Sanitizer
NDC: 21532-1410 | Form: LIQUID
Manufacturer: Bunzl Processor Distribution LLC
Category: otc | Type: HUMAN OTC DRUG LABEL
Date: 20181205

ACTIVE INGREDIENTS: ALCOHOL 70 mL/100 mL
INACTIVE INGREDIENTS: WATER; GLYCERIN

Drug Facts

Active Ingredients

Ethyl Alcohol 70% (v/v)

Purpose

Hand Sanitizer

Uses

Hand wash to help reduce bacteria that potentially can cause diseases

Helps prevent cross contamination by hand contact

Helps prevent drying and chafing of skin

Recommended for repeated use

Warnings

For External use only

Flammable, keep away from fire or flame

When using this product

Do not use in or near eyes

Use in well-ventilated area

Discontinue use if irritation and/or redness develops

Keep out of reach of children.

In case of accidental ingestion, seek medical attention or contact Poison Control Center immediately

Directions

Wet hands thoroughly with product, covering entire surface of hands, including fingertips, cuticles, wrists and forearms

Rub vigorously into skin until dry

No rinsing or toweling required

STORAGE AND HANDLING

Store in a cool dry place below 104 F

For Food Processing, Food Service and Professional Use Only

NDC 21532-1410-1

Inactive Ingredients

Purified Water, Glycerin

PACKAGE LABEL

SaniKleen

E3 Hand Sanitizer

Marketed By:

Bunzl

528 East 19th Avenue

North Kansas City, MO 64116

CONTENTS: 1 Gallon